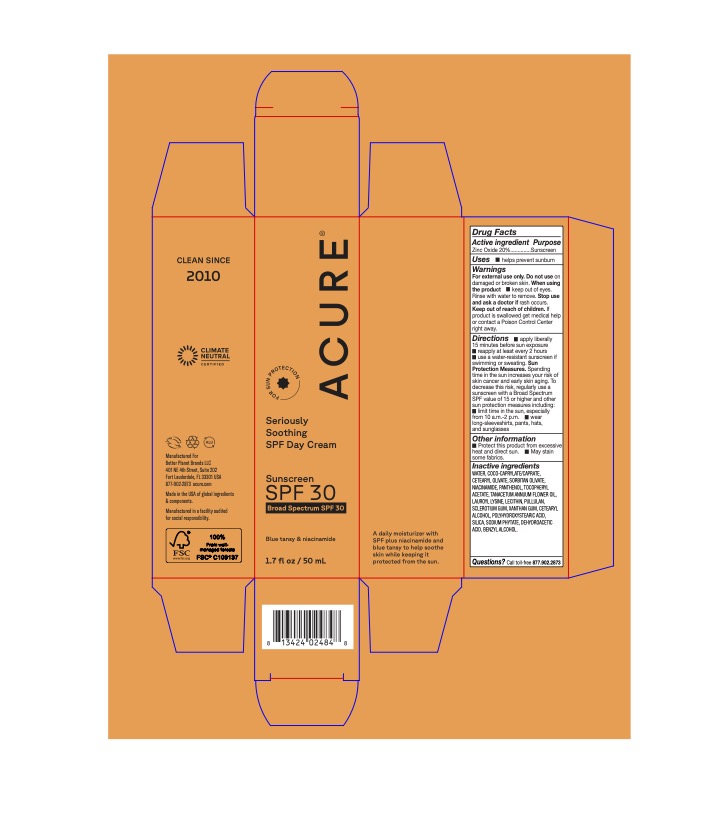 DRUG LABEL: Seriously Soothing SPF Day Cream
NDC: 54136-179 | Form: CREAM
Manufacturer: Better Planet Brands LLC
Category: otc | Type: HUMAN OTC DRUG LABEL
Date: 20251203

ACTIVE INGREDIENTS: ZINC OXIDE 20 g/100 g
INACTIVE INGREDIENTS: LAUROYL LYSINE; LECITHIN, SOYBEAN; BENZYL ALCOHOL; COCO-CAPRYLATE/CAPRATE; TANACETUM ANNUUM FLOWERING TOP OIL; PANTHENOL; POLYHYDROXYSTEARIC ACID (2300 MW); TOCOPHEROL; BETASIZOFIRAN; CETEARYL GLUCOSIDE; GLYCERIN; PULLULAN; SORBITAN OLIVATE; XANTHAN GUM; CETEARYL OLIVATE; CETOSTEARYL ALCOHOL; WATER; SILICON DIOXIDE; DEHYDROACETIC ACID; NIACINAMIDE; HEXASODIUM PHYTATE

Seriously Soothing SPF 30 Face Cream

Active ingredients

Zinc Oxide 15.50%

Purpose

Sunscreen

Uses

* Help prevent sunburn * if used as directed with other sun protection measures (see Directions), decreases the risk of skin cancer and early skin aging caused by the sun.

Warnings

For external use only.

Do not useon damaged or broken skin.

WHEN USING

When using the product* keep out of eyes. Rinse with water to remove.

Stop use and ask a doctorif rash occurs.

Keep out of reach of children.If product is swallowed get medical help or contact a Poison Control Center right away.

May stain some fabrics.

Directions

• apply liberally 15 minutes before sun exposure reapply at least every 2 hours use a water-resistant sunscreen if

swimming or sweating. Sun Protection Measures. Spending time in the sun increases your risk of skin cancer and early skin aging. To decrease this risk, regularly use a sunscreen with a Broad Spectrum SPF value of 15 or higher and other sun protection measures including:

• limit time in the sun, especially from 10 a.m.-2 p.m.

wear long-sleeveshirts, pants, hats, and sunglasses

Other information

Protect this product from excessive heat and direct sun. • May stain some fabrics.

Inactive Ingredients

WATER, COCO-CAPRYLATE/CAPRATE, CELEARYL OLIVATE, SORBITAN OLIVATE, NIACINAMIDE, PANTHENOL, TOCOPHERYL ACETATE, TANACETUM ANNUUM FLOWER OIL, LAUROYL LYSINE, LECITHIN, PULLULAN, SCLEROTIUM GUM, XANTHAN GUM, CETEARYL ALCOHOL, POLYHYDROXYSTEARIC ACID, SILICA, SODIUM PHYTATE, DEHYDROACETIC ACID, BENZYL ALCOHOL

Questions?

Call toll-free 877.902.2873